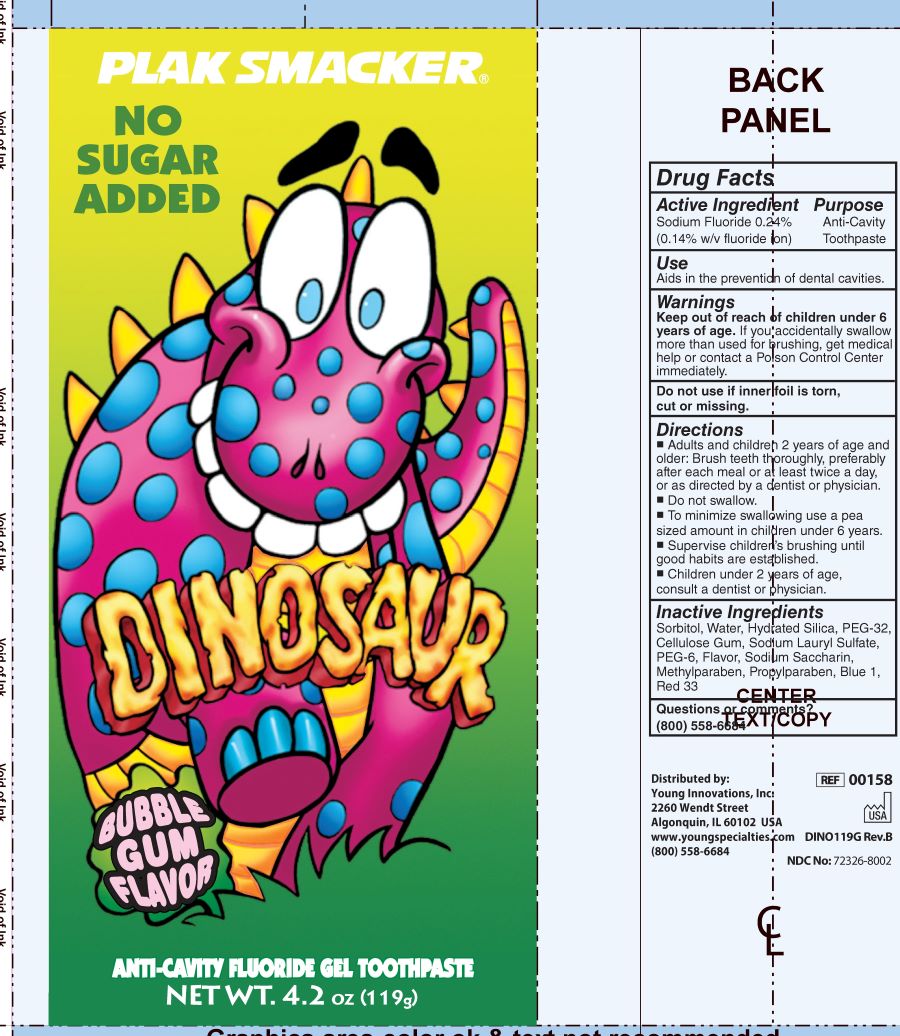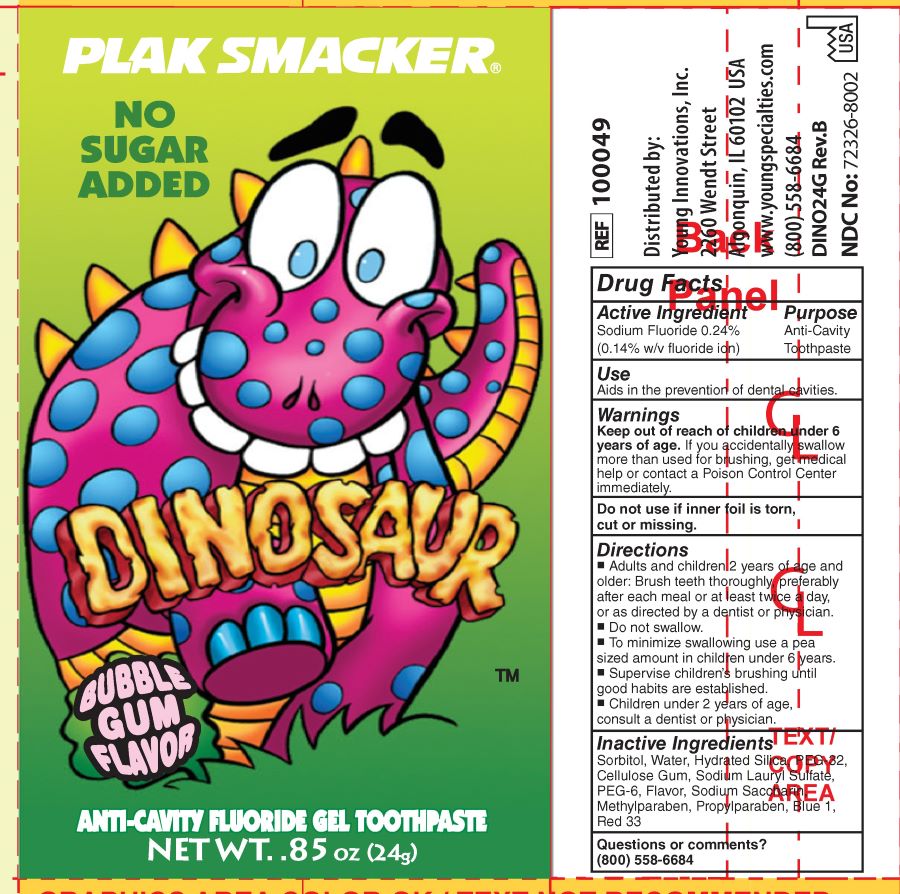 DRUG LABEL: Plak Smacker Anti Cavity Fluoride
NDC: 72326-8002 | Form: PASTE
Manufacturer: YOUNG PS ACQUISITION, LLC
Category: otc | Type: HUMAN OTC DRUG LABEL
Date: 20231016

ACTIVE INGREDIENTS: SODIUM FLUORIDE 1.4 mg/1 g
INACTIVE INGREDIENTS: POLYETHYLENE GLYCOL 1450; HYDRATED SILICA; SACCHARIN SODIUM; WATER; SODIUM LAURYL SULFATE; SORBITOL; POLYETHYLENE GLYCOL 300; CARBOXYMETHYLCELLULOSE; PROPYLPARABEN; METHYLPARABEN; FD&C BLUE NO. 1; D&C RED NO. 33

Plak Smacker DINOSAUR ANTI-CAVITY FLUORIDE GEL TOOTHPASTE

Active Ingredient

Sodium Fluoride 0.24% (0.14% w/v Fluoride ion)

Purpose

Anticavity toothpaste

Purpose

Anti-Cavity Toothpaste

Use

Aids in the prevention of dental cavities.

Warnings

Keep out of the reach of children under 6 years of age.If more than used for brushing is accidentally swallowed, get medical help or contact a Poison Control Center right away.

Do not use if inner foil is torn, cut, or missing.

Keep out of reach of children.

KEEP OUT OF REACH OF CHILDREN

Keep out of the reach of children under 6 years of age. If you accidentally swallow more than used for brushing, get medical help or contact a Poison Control Center immediately.

Do not use if inner foil is torn, cut or missing.

Directions

- Adults and children 2 years of age and older: Brush teeth thoroughly, preferably after each meal or at least twice a day, or as directed by a dentist or physician.
- Do not swallow
- To minimize swallowing use a pea sized amount in children under 6 years.
- Supervise children's brushing until good habits are established.
- Children under 2 years of age, consult a dentist or physician.

Inactive Ingredients

Sorbitol, Water, Hydrated silica, PEG-32, Cellulose Gum, Sodium Lauryl Sulfate, PEG-6, Flavor, Sodium Saccharin, Methylparaben, Propyparaben, Blue1, Red 33

Questions or comments?

(800) 558-6684

PACKAGE LABEL

PLAK SMACKER®

NO SUGAR ADDED

DINOSAUR

BUBBLE GUM FLAVOR

ANTI-CAVITY FLUORIDE GEL TOOTHPASTE

NET WT. 4.2 oz (119g)